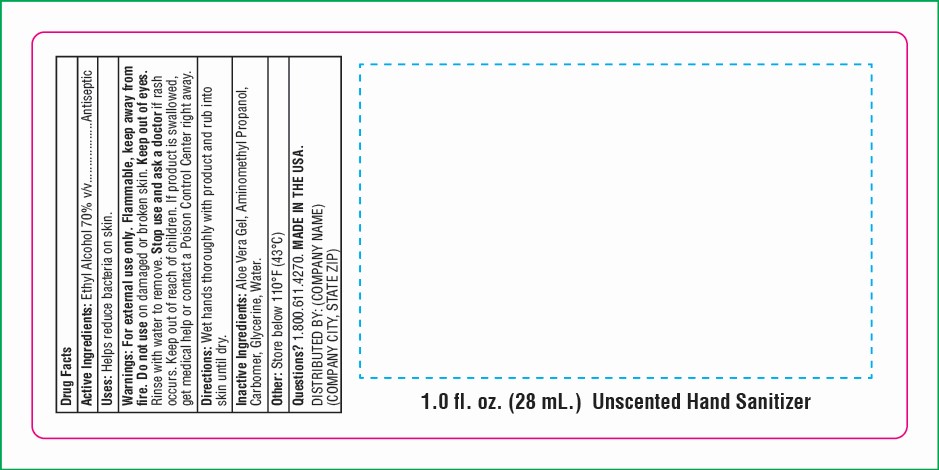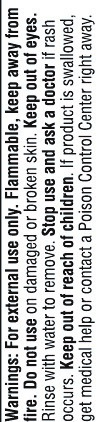 DRUG LABEL: SnugZ Hand Sanitizing Spry
NDC: 76309-451 | Form: SPRAY
Manufacturer: SnugZ/USA, LLC
Category: otc | Type: HUMAN OTC DRUG LABEL
Date: 20251229

ACTIVE INGREDIENTS: ALCOHOL 70 mL/100 mL
INACTIVE INGREDIENTS: WATER; AMINOMETHYL PROPANEDIOL; CARBOMER 940; ALOE VERA LEAF POLYSACCHARIDES; GLYCERIN

ZS - Hand Sanitizer Spray

Active Ingredient: Ethyl Alcohol 70% v/v

PURPOSE

Antiseptic

INACTIVE INGREDIENT

Inactive Ingredients: Aloe Vera Gel, Aminomethyl Propanol, Carbomer, Clycerine, Water

DOSAGE AND ADMINISTRATION

Wet hands thoroughly with product and rub into skin until dry.

INDICATIONS AND USAGE

Helps reduce bacteria on skin.